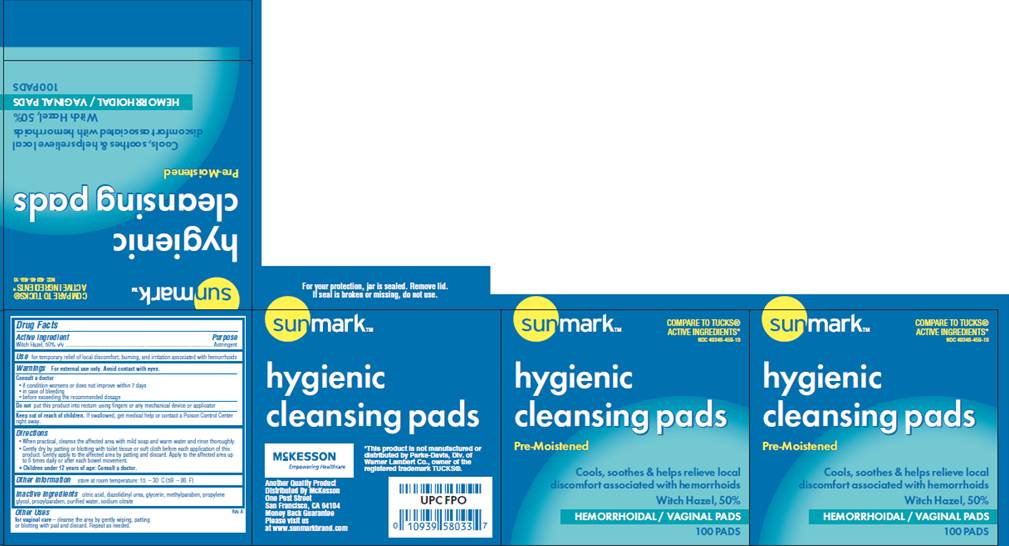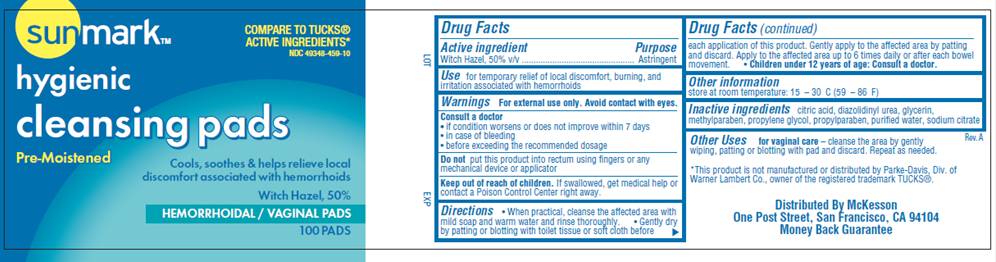 DRUG LABEL: Hygienic Cleansing Pads
NDC: 49348-459 | Form: SOLUTION
Manufacturer: McKesson
Category: otc | Type: HUMAN OTC DRUG LABEL
Date: 20100204

ACTIVE INGREDIENTS: witch hazel 0.50 mL/1 mL
INACTIVE INGREDIENTS: citric acid monohydrate; diazolidinylurea; glycerin; methylparaben; propylene glycol; propylparaben; sodium citrate; water

DRUG FACTS

ACTIVE INGREDIENT

Witch Hazel 50% v/v

PURPOSE

Astringent

USE

For temporary relief of local discomfort, burning, and irritation associated with hemorrhoids

WARNINGS

For external use only. Avoid contact with eyes.

Consult a doctor

- if condition worsens or does not improve within 7 days
- in case of bleeding
- before exceeding the recommended dosage

Do not

put this product into rectum using fingers or any mechanical device or applicator

Keep out of reach of children

If swallowed, get medical help or contact a Poison Control Center right away.

DIRECTIONS

- When practical, cleanse the affected area with mild soap and warm water and rinse thoroughly.
- Gently dry by patting or blotting with toilet tissue or soft cloth before each application of this product. Gently apply to the affected area by patting and then discard. Apply to the affected area up to 6 times daily or after each bowel movement.
- Children under 12 years of age: consult a doctor.

OTHER INFORMATION

Store at room temperature: 15°- 30° C (59° - 86° F)

Other Uses

for vaginal care - cleanse the area by gently wiping, patting or blotting with pad and discard. Repeat as needed

INACTIVE INGREDIENTS

citric acid, diazolidinyl urea, glycerin, methylparaben, propylene glycol, propylparaben, purified water, sodium citrate

PACKAGE INFORMATION - 100 COUNT JAR This package is a representation. Packaging is similar for other sizes available.

Sunmark®

COMPARE TO TUCKS® ACTIVE INGREDIENTS*
NDC 49348-459-10

hygienic cleansing pads
Pre-Moistened
Cools, soothes and helps relieve local discomfort associated with hemorrhoids
Witch Hazel, 50%
HEMORRHOIDAL / VAGINAL PADS
100 PADS
*This product is not manufactured or distributed by Parke-Davis, Div. of Warner Lambert Co., owner of the registered trademark TUCKS®.
Distributed by McKesson
One Post Street, San Francisco, CA 94104
Money Back Guarantee

PACKAGE INFORMATION - 100 COUNT CARTON This package is a representation. Packaging is similar for other sizes available.

Sunmark®
COMPARE TO TUCKS® ACTIVE INGREDIENTS*
NDC 49348-459-10

hygienic cleansing pads
Pre-Moistened
Cools, soothes and helps relieve local discomfort associated with hemorrhoids
Witch Hazel, 50%
HEMORRHOIDAL / VAGINAL PADS
100 PADS

For your protection, jar is sealed. Remove lid. If seal is broken or missing, do not use.

*This product is not manufactured or distributed by Parke-Davis, Div. of Warner Lambert Co., owner of the registered trademark TUCKS®.
Another Quality Product
Distributed by McKesson
One Post Street
San Francisco, CA 94104
Money Back Guarantee

Please visit us at www.sunmarkbrand.com